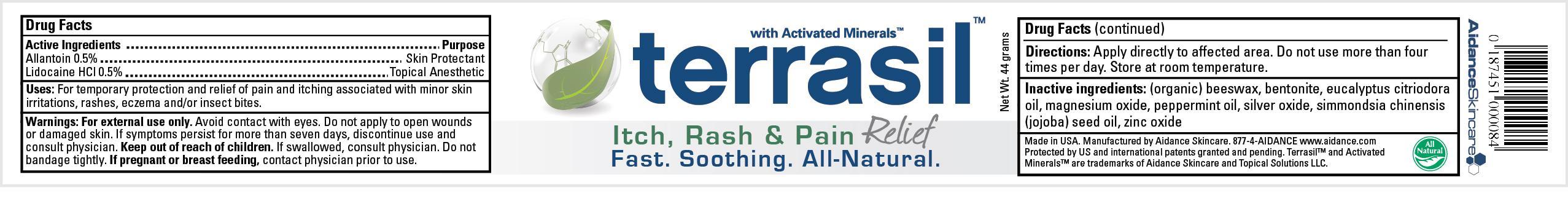 DRUG LABEL: Terrasil Itch, Rash and Pain Relief
NDC: 24909-123 | Form: OINTMENT
Manufacturer: Aidance Skincare & Topical Solutions, LLC
Category: otc | Type: HUMAN OTC DRUG LABEL
Date: 20120905

ACTIVE INGREDIENTS: Allantoin 0.5 g/100 g; Lidocaine Hydrochloride 0.5 g/100 g
INACTIVE INGREDIENTS: BENTONITE; EUCALYPTUS OIL; JOJOBA OIL; MAGNESIUM OXIDE; PEPPERMINT OIL; SILVER OXIDE; WHITE WAX; ZINC OXIDE

Drug Facts

Active Ingredients

Allantoin 0.5%, Lidocaine HCL 0.5%

Purpose

Allantoin - Skin Protectant

Lidocaine HCL - Topical Anesthetic

Uses

For temporary protection and relief of pain and itching associated with minor skin irritations, rashes, eczema and/or insect bites.

Warnings

For external use only. Avoid contact with eyes. Do not apply to open wounds
or damaged skin. If symptoms persist for more than seven days, discontinue use and
consult physician. If swallowed, consult physician. Do not bandage tightly.
If pregnant or breast feeding, contact physician prior to use.

Keep out of reach of children.

If swallowed, consult physician.

Directions

Apply directly to effected area. Do not use more than four
times per day. Store at room temperature.

Inactive Ingredients

(Organic) Beeswax, Bentonite, Eucalyptus Citriodora Oil, Magnesium Oxide, Peppermint Oil, Silver Oxide, Simmondsia Chinensis (Jojoba) Seed Oil,
Zinc Oxide.